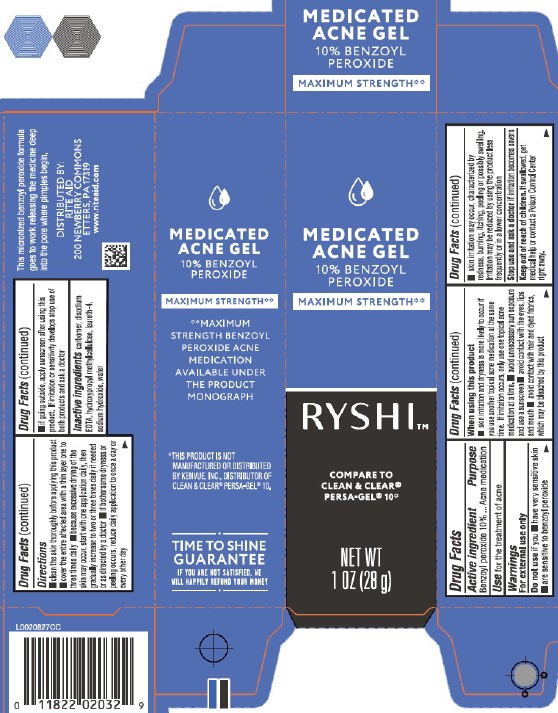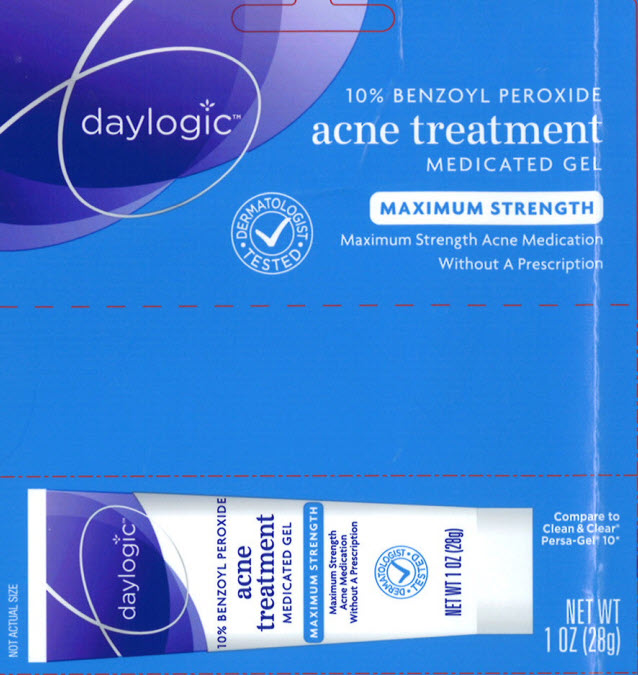 DRUG LABEL: Acne Treatment
NDC: 11822-7701 | Form: GEL
Manufacturer: Rite Aid Corporation
Category: otc | Type: HUMAN OTC DRUG LABEL
Date: 20260130

ACTIVE INGREDIENTS: BENZOYL PEROXIDE 100 mg/1 g
INACTIVE INGREDIENTS: CARBOMER HOMOPOLYMER, UNSPECIFIED TYPE; EDETATE DISODIUM; HYPROMELLOSES; LAURETH-4; SODIUM HYDROXIDE; WATER

RYSHI_Daylogic 229.001/229AC-AD
10% Benzoyl Peroxide Acne Medicated Gel

Active ingredients

Benzoyl peroxide 10%

Purpose

Acne medication

Use

for the treatment of acne

Warnings

For external use only

Do not use

if you

- have very sensitive skin
- are sensitive to benzoyl peroxide

When using this product

- skin irritation and dryness is more likely to occur if you use another topical acne medication at the same time. If irritation occurs, only use one topical acne medication at a time
- avoid unnecessary sun exposure and use a sunscreen
- avoid contact with eyes, lips and mouth
- avoid contact with hair and dyed fabrics, which may be bleached by this product
- skin irritation may occur, characterized by redness, burning, itching, peeling or possible swelling. Irritation may be reduced by using the product less frequently or in a lower concentration

Stop use and ask a doctor if

irritation becomes severe

Keep out of reach of children.

If swallowed, get medical help or contact a Poison Control Center right away.

Directions

- clean the skin thoroughly before applying this product
- cover the entire affected area with a thin layer one to three times daily
- because excessive drying of the skin may occur, start with one application daily, then gradually increase to two or three times daily if needed or as directed by a doctor
- if bothersome dryness or peeling occurs, reduce daily application to once a day or every other day
- if going outside, apply sunscreen after using this product. If irritation or sensitivity develops stop use of both products and ask a doctor

Inactive ingredients

carbomer, disodium EDTA, hydroxypropyl methylcellulose, laureth-4, sodium hydroxide, water

Side panel claims

MEDICATED ACNE GEL

10% BENZOYL PEROXIDE

MAXIMUM STRENGTH**

**MAXIMUM STRENGTH BENZOYL PEROXIDE ACNE MEDICATION AVAILABLE UNDER THE PRODUCT MONOGRAPH

*THIS PRODUCT IS NOT MANUFACTURED OR DISTRIBUTED BY KENVUE, INC., DISTRIBUTER OF CLEAN & CLEAR® PERSA-GEL® 10.

TIME TO SHINE GUARANTEE

IF YOU ARE NOT SATISFIED, WE WILL HAPPILY REFUND YOUR MONEY.

Claims

This micronized benzoyl peroxide formula goes to work releasing the medicine deep into the pore where pimples begin.

Adverse reaction

DISTRIBUTED BY:

RITE AID

200 NEWBERRY COMMONS

ETTERS, PA 17319

www.riteaid.com

Principal display panel

MEDICATED ACNE GEL

10% BENZOYL PEROXIDE

MAXIMUM STRENGTH**

RYSHI™

COMPARE TO CLEAN & CLEAR® PERSA-GEL® 10*

NET WT 1 OZ (28 g)

Principal display panel

daylogic

10% BENZOYL PEROXIDE

acne treatment

MEDICATED GEL

MAXIMUM STRENGTH

Maximum Strength Acne Medication Without A Prescription

DERMATOLOGIST TESTED

Compare to clean & Clear Persa-Gel 10.*

NET WT 1 OZ (28 g)